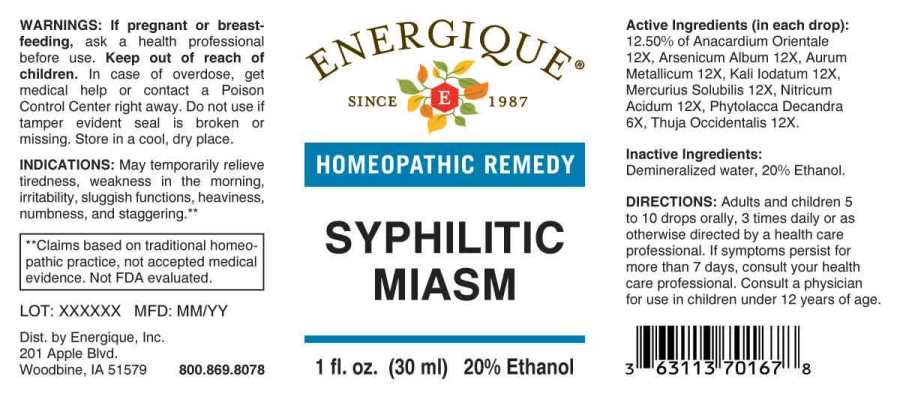 DRUG LABEL: Syphilitic Miasm
NDC: 44911-0482 | Form: LIQUID
Manufacturer: Energique, Inc.
Category: homeopathic | Type: HUMAN OTC DRUG LABEL
Date: 20241030

ACTIVE INGREDIENTS: PHYTOLACCA AMERICANA ROOT 6 [hp_X]/1 mL; SEMECARPUS ANACARDIUM JUICE 12 [hp_X]/1 mL; ARSENIC TRIOXIDE 12 [hp_X]/1 mL; GOLD 12 [hp_X]/1 mL; POTASSIUM IODIDE 12 [hp_X]/1 mL; MERCURIUS SOLUBILIS 12 [hp_X]/1 mL; NITRIC ACID 12 [hp_X]/1 mL; THUJA OCCIDENTALIS LEAFY TWIG 12 [hp_X]/1 mL
INACTIVE INGREDIENTS: WATER; ALCOHOL

DRUG FACTS:

ACTIVE INGREDIENTS:

(in each drop): 12.50% of Phytolacca Decandra 6X, Anacardium Orientale 12X, Arsenicum Album 12X, Aurum Metallicum 12X, Kali Iodatum 12X, Mercurius Solubilis 12X, Nitricum Acidum 12X, Thuja Occidentalis 12X.

INDICATIONS:

May temporarily relieve tiredness, weakness in the morning, irritability, sluggish functions, heaviness, numbness, and staggering.**

**Claims based on traditional homeopathic practice, not accepted medical evidence. Not FDA evaluated.

WARNINGS:

If pregnant or breast-feeding, ask a health professional before use.

Keep out of reach of children. In case of overdose, get medical help or contact a Poison Control Center right away.

Do not use if tamper evident seal is broken or missing. Store in a cool, dry place.

Keep out of reach of children. In case of overdose, get medical help or contact a Poison Control Center right away.

DIRECTIONS:

Adults and children 5 to 10 drops orally, 3 times daily or as otherwise directed by a health care professional. If symptoms persist for more than 7 days, consult your health care professional. Consult a physician for use in children under 12 years of age.

INDICATIONS:

May temporarily relieve tiredness, weakness in the morning, irritability, sluggish functions, heaviness, numbness, and staggering.**

**Claims based on traditional homeopathic practice, not accepted medical evidence. Not FDA evaluated.

INACTIVE INGREDIENTS:

Demineralized water, 20% Ethanol.

QUESTIONS:

Dist. by Energique, Inc.

201 Apple Blvd

Woodbine, IA 51579 800-869-8078

PACKAGE LABEL DISPLAY:

ENERGIQUE

SINCE 1987

HOMEOPATHIC REMEDY

SYPHILITIC

MIASM

1 fl. oz. (30 ml)